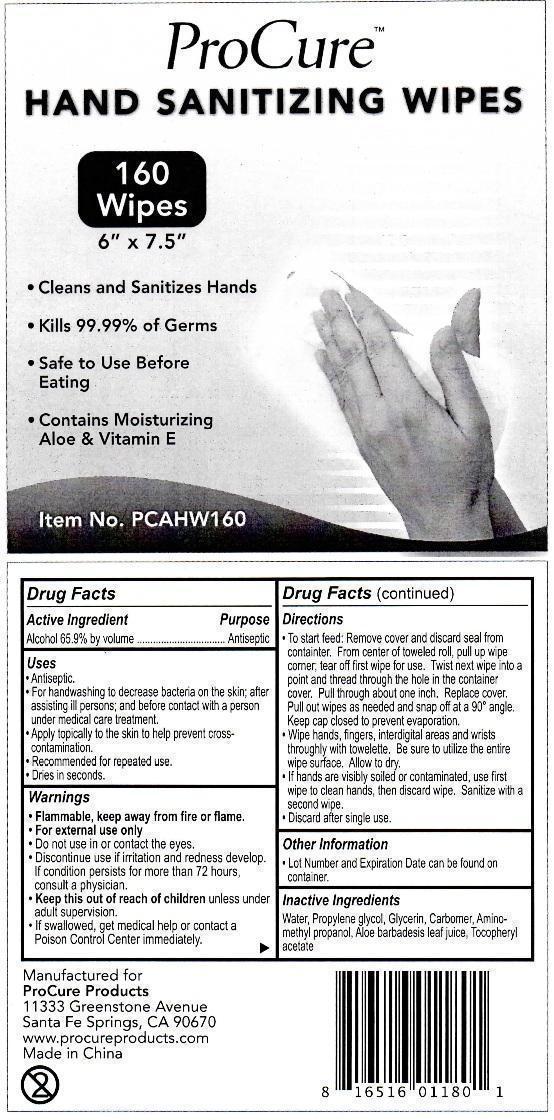 DRUG LABEL: ProCure Hand Sanitizing
NDC: 57544-180 | Form: SWAB
Manufacturer: TwinMed, LLC
Category: otc | Type: HUMAN OTC DRUG LABEL
Date: 20201118

ACTIVE INGREDIENTS: ALCOHOL 65.9 g/100 g
INACTIVE INGREDIENTS: WATER; PROPYLENE GLYCOL; GLYCERIN; AMINOMETHYLPROPANOL; ALOE VERA LEAF; .ALPHA.-TOCOPHEROL ACETATE

Pro Cure Hand Sanitizing Wipes

ACTIVE INGREDIENT

ALCOHOL 65.9% BY VOLUME

PURPOSE

Antiseptic

Uses

- Antiseptic

- For handwashing to decrease bacteria on the skin; after assisting ill persons; and before contact with a person under medical care treatment

- Apply topically to the skin to hep prevent cross-contamination

- Recommended for repeated use.

- Dries in seconds

WARNINGS

Flammable, keep away from fire and flame

For extermal use only.

Do not use

in or contact the eyes

Discontinue use

If irritation and redness develop. If condition persists for more than 72 hours, consult a physician.

Keep this out of reach of children

unless under adult supervision.

If swallowed, get medical hep or contact a Poison Control Center immediately.

Directions

To start feed: REmove cover and discard seal from container. From center of toweled roll, pull up wipe corner; tear off first wipe for use. Twist next wipe into a point and thread through hole in the container cover. Pull thrugh about one inch. Replace cover. Pull out wipes as needed and sanp off at a 90 degree angle. Keep cap closed to prevent evaporation.

Wipe hands, fingers, interdigital areas and wrists thoroughly with towelette. Be sure to utilize the entire wipe surface. Allow to dry.

If hands are visibly soiled or contaminated, use first wipe to clean hands, then discard wipe. Sanitize with a second wipe.

Discard after single use.

Other Information

Lot Number and Expiration Date can be found on container

Inactive Ingredients

Water, Propylene glycol, Glycerin, Carbomer, Aminomethylpropanol, Aloe barbadensis leaf juice, Tocopheryl acetate.